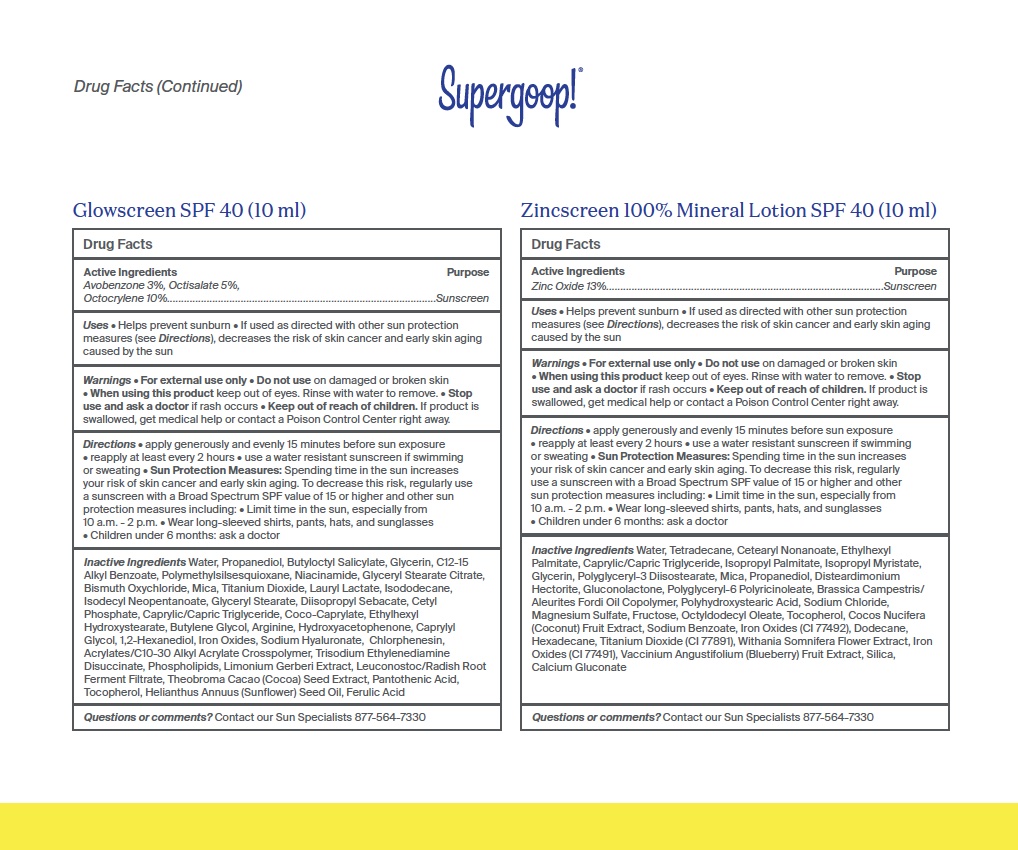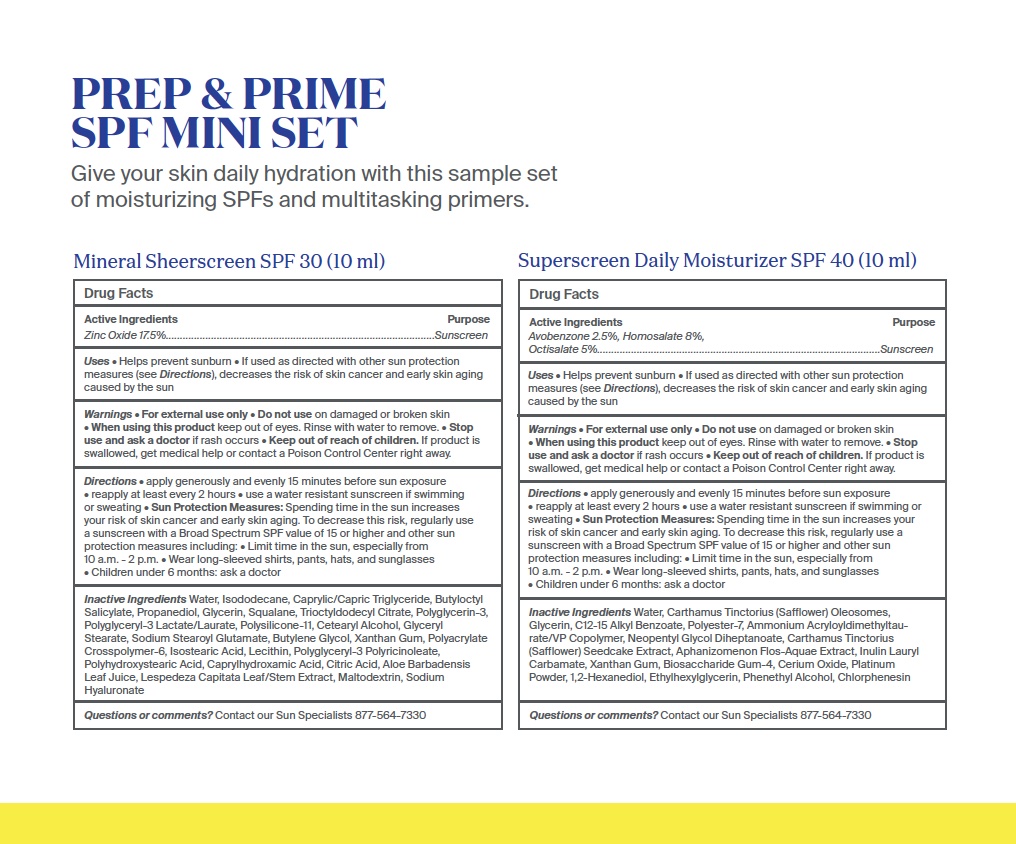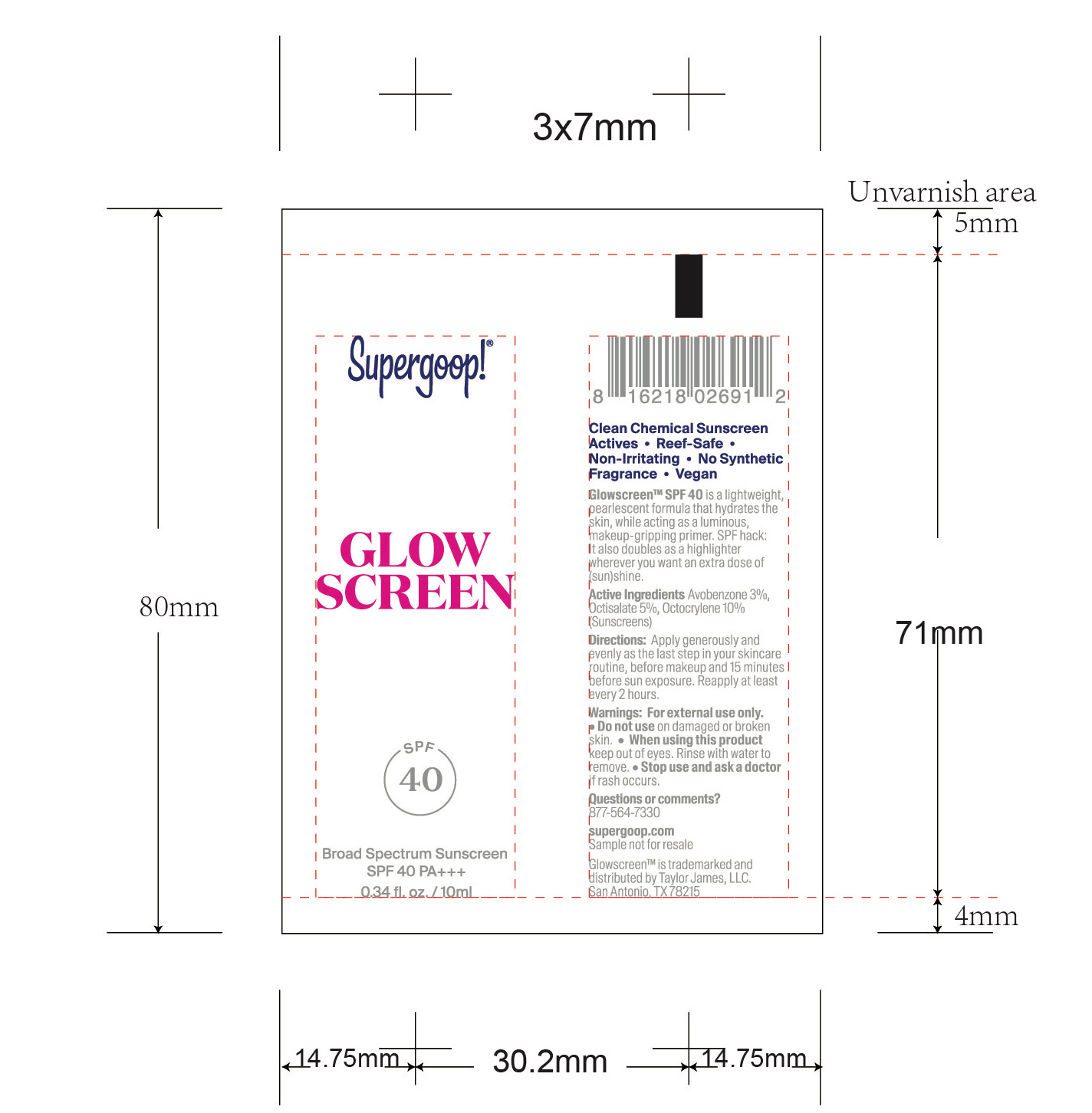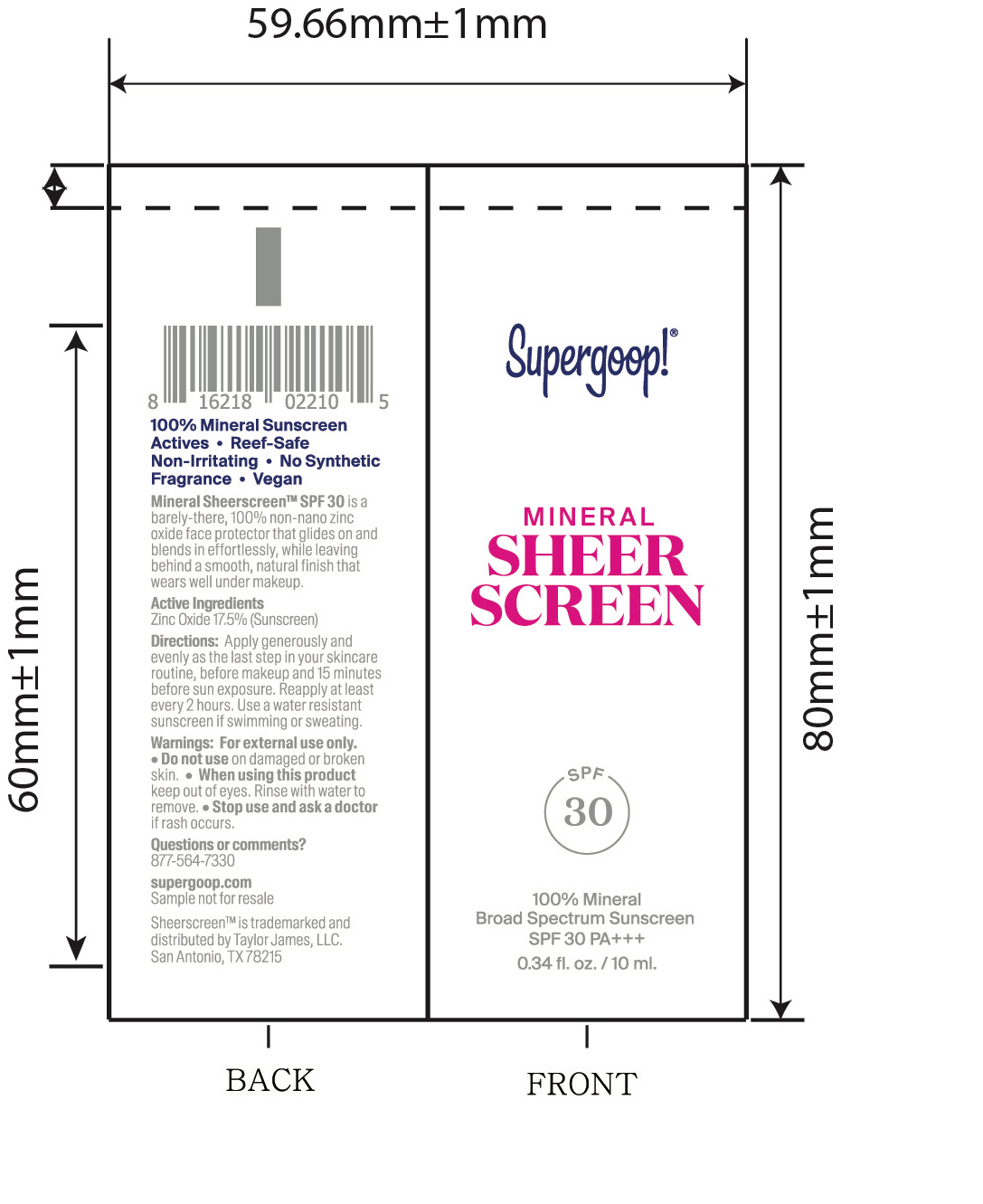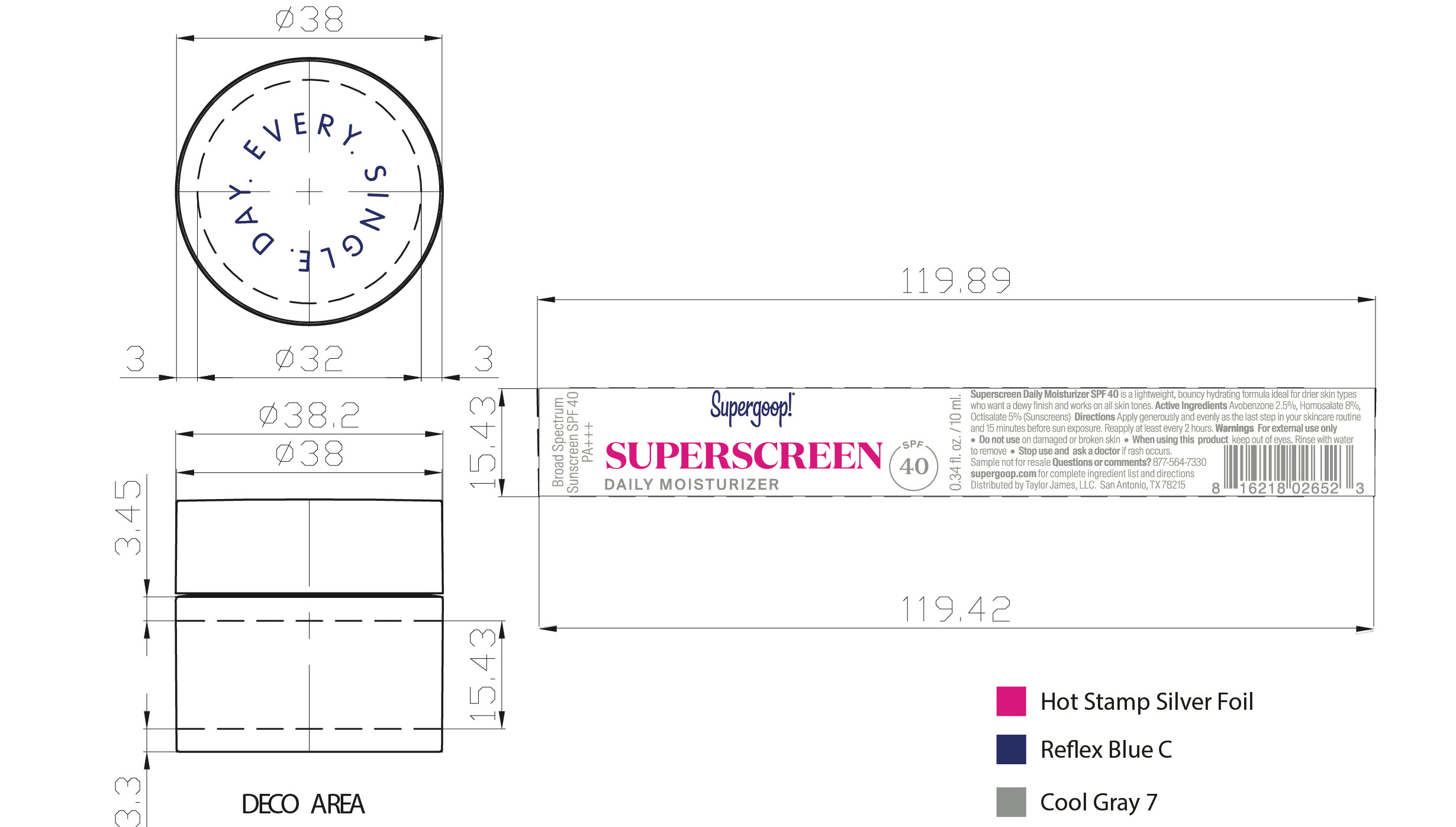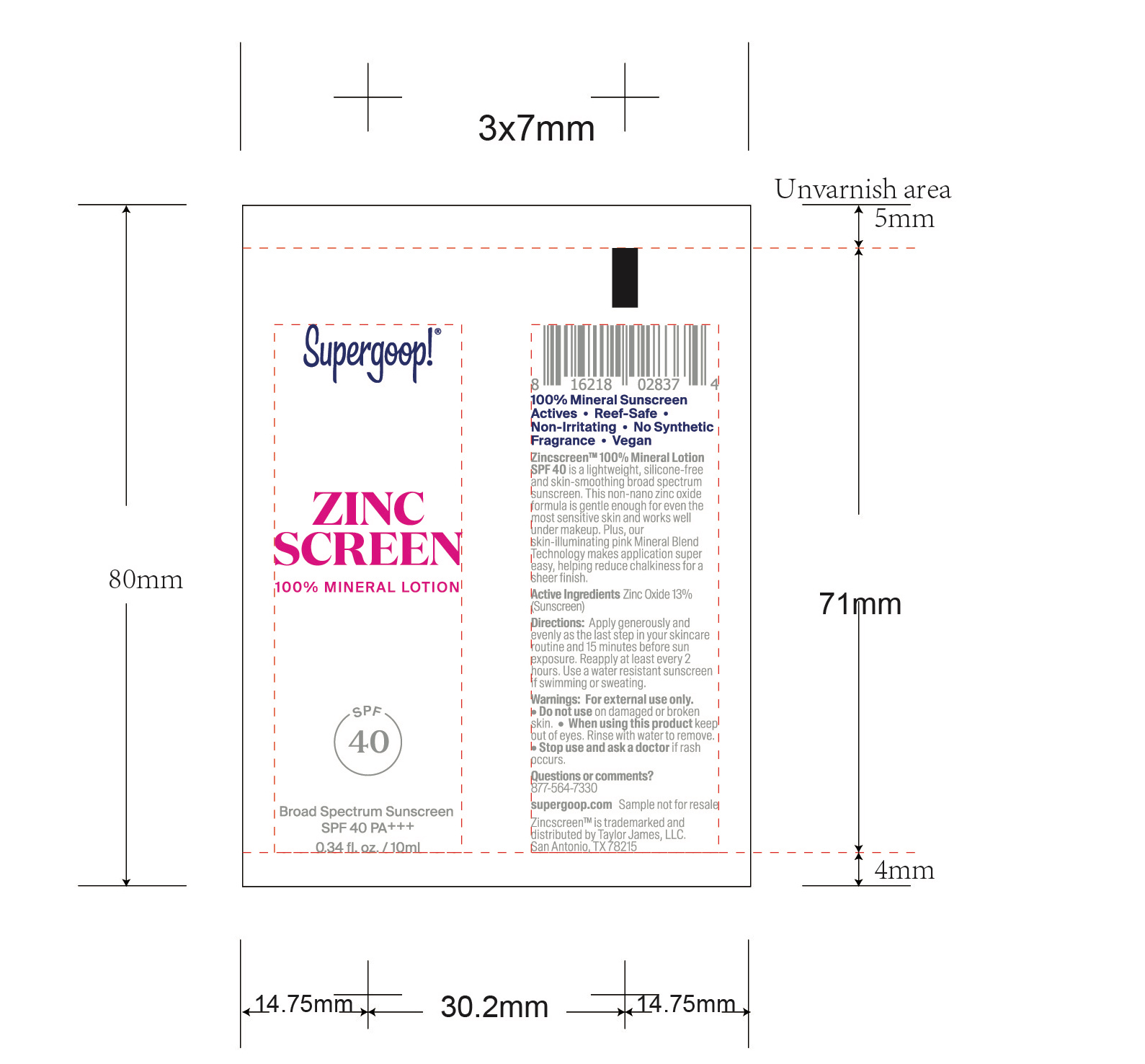 DRUG LABEL: Prep and Prime SPF Mini Set
NDC: 82384-0005 | Form: KIT | Route: TOPICAL
Manufacturer: System Beauty, LLC
Category: otc | Type: HUMAN OTC DRUG LABEL
Date: 20211206

ACTIVE INGREDIENTS: ZINC OXIDE 17.5 g/100 mL; HOMOSALATE 8 g/100 mL; AVOBENZONE 2.5 g/100 mL; OCTISALATE 5 g/100 mL; OCTISALATE 5 g/100 mL; AVOBENZONE 3 g/100 mL; OCTOCRYLENE 10 g/100 mL; ZINC OXIDE 13 g/100 mL
INACTIVE INGREDIENTS: BUTYLOCTYL SALICYLATE; GLYCERYL MONOSTEARATE; SODIUM STEAROYL GLUTAMATE; BUTYLENE GLYCOL; XANTHAN GUM; AMMONIUM ACRYLOYLDIMETHYLTAURATE, DIMETHYLACRYLAMIDE, LAURYL METHACRYLATE AND LAURETH-4 METHACRYLATE COPOLYMER, TRIMETHYLOLPROPANE TRIACRYLATE CROSSLINKED (45000 MPA.S); LECITHIN, SOYBEAN; POLYGLYCERYL-3 PENTARICINOLEATE; POLYHYDROXYSTEARIC ACID (2300 MW); CITRIC ACID MONOHYDRATE; MEDIUM-CHAIN TRIGLYCERIDES; GLYCERIN; TRIOCTYLDODECYL CITRATE; ISOSTEARIC ACID; WATER; POLYGLYCERIN-3; DIMETHICONE/VINYL DIMETHICONE CROSSPOLYMER (SOFT PARTICLE); SQUALANE; CETOSTEARYL ALCOHOL; ISODODECANE; PROPANEDIOL; ALOE VERA LEAF; CAPRYLHYDROXAMIC ACID; MALTODEXTRIN; HYALURONATE SODIUM; CARTHAMUS TINCTORIUS SEEDCAKE; CERIC OXIDE; ETHYLHEXYLGLYCERIN; 1,2-HEXANEDIOL; PHENYLETHYL ALCOHOL; CARTHAMUS TINCTORIUS SEED OLEOSOMES; WATER; POLYESTER-7; APHANIZOMENON FLOSAQUAE; BIOSACCHARIDE GUM-4; PLATINUM; CHLORPHENESIN; NEOPENTYL GLYCOL DIHEPTANOATE; XANTHAN GUM; GLYCERIN; ALKYL (C12-15) BENZOATE; AMMONIUM ACRYLOYLDIMETHYLTAURATE/VP COPOLYMER; 1,2-HEXANEDIOL; CHLORPHENESIN; ARGININE; CETYL PHOSPHATE; COCO-CAPRYLATE; HYDROXYACETOPHENONE; TOCOPHEROL; ALKYL (C12-15) BENZOATE; NIACINAMIDE; MICA; WATER; BUTYLOCTYL SALICYLATE; BISMUTH OXYCHLORIDE; TITANIUM DIOXIDE; PROPANEDIOL; GLYCERIN; POLYMETHYLSILSESQUIOXANE (4.5 MICRONS); CAPRYLYL GLYCOL; TRISODIUM ETHYLENEDIAMINE DISUCCINATE; SUNFLOWER OIL; FERRIC OXIDE RED; HYALURONATE SODIUM; LECITHIN, SOYBEAN; LAURYL LACTATE; ETHYLHEXYL HYDROXYSTEARATE; BUTYLENE GLYCOL; CARBOMER INTERPOLYMER TYPE A (ALLYL SUCROSE CROSSLINKED); LEUCONOSTOC/RADISH ROOT FERMENT FILTRATE; COCOA; FERULIC ACID; MEDIUM-CHAIN TRIGLYCERIDES; GLYCERYL STEARATE CITRATE; ISODODECANE; ISODECYL NEOPENTANOATE; GLYCERYL MONOSTEARATE; DIISOPROPYL SEBACATE; LIMONIUM GERBERI WHOLE; PANTOTHENIC ACID; CETEARYL NONANOATE; MAGNESIUM SULFATE ANHYDROUS; FRUCTOSE; OCTYLDODECYL OLEATE; DODECANE; TOCOPHEROL; SODIUM BENZOATE; CALCIUM GLUCONATE; MICA; PROPANEDIOL; DISTEARDIMONIUM HECTORITE; HEXADECANE; FERRIC OXIDE RED; ETHYLHEXYL PALMITATE; MEDIUM-CHAIN TRIGLYCERIDES; POLYGLYCERYL-3 DIISOSTEARATE; ISOPROPYL PALMITATE; GLUCONOLACTONE; POLYHYDROXYSTEARIC ACID (2300 MW); SODIUM CHLORIDE; COCONUT; WATER; TETRADECANE; ISOPROPYL MYRISTATE; GLYCERIN; FERRIC OXIDE YELLOW; TITANIUM DIOXIDE; WITHANIA SOMNIFERA FLOWER; LOWBUSH BLUEBERRY; SILICON DIOXIDE

Prep and Prime SPF Mini Set

Mineral Sheerscreen SPF 30

Active ingredients Purpose

Zinc Oxide 17.5% Sunscreen

Superscreen Daily Moisturizer SPF 40

Active Ingredients Purpose

Avobenzone 2.5% Sunscreen

Homosalate 8% Sunscreen

Octisalate 5% Sunscreen

Glowscreen SPF 40

Active Ingredients Purpose

Avobenzone 3% Sunscreen

Octisalate 5% Sunscreen

Octocrylene10% Sunscreen

Zincsreen 100% Mineral Lotion SPF 40

Active Ingredients Purpose

Zinc Oxide 13% Sunscreen

Uses

- Helps prevent sunburn
- If used as directed with other sun protection measures (see Directions), decreases the risk of skin cancer and early skin aging caused by the sun

Keep out of reach of children. If product is swallowed, get medical help or contact a Poison Control Center right away.

Stop use and ask a doctor if rash occurs

Warnings

For external use only

Do not use on damaged or broken skin

When using this product keep out of eyes

Directions

- apply generously and evenly 15 minutes before sun exposure
- reapply at least every 2 hours
- Use a water resistant sunscreen if swimming or sweating

Sun Protection Measure Spending time in the sun increases your risk of skin cancer and early skin aging. To decrease this risk, regularly use a sunscreen with a Broad Spectrum value of 15 or higher and other sun protection measures including:

- Limit time in the sun, especially from 10 a.m. - 2p.m.
- Wear Long-sleeved shirts, pants hats and sunglasses
- Children under 6 months ask a doctor

Mineral Sheerscreen Broad Spectrum Sunscreen SPF 30

Water, Isododecane, Caprylic/Capric Triglyceride, Butyloctyl Salicylate, Propanedlol, Glycerin, Squalane, Trioctyldodecyl Citrate, Polyglycerln-3, Polyglyceryl-3 Lactate/Laurate, Polysilicone-11, Cetearyl Alcohol, Glyceryl Stearate, Sodium Stearoyl Glutamate, Butylene Glycol, Xanthan Gum, Polyacrylate Crosspolymer-6, lsostearic Acid, Lecithin, Polyglyceryl-3 Polyricinoleate, Polyhydroxystearic Acid, Caprylhydroxamic Acid, Citric Acid, Aloe Barbadensis Leaf Juice, Lespedeza Capitata Leaf/Stem Extract, Maltodextrin, Sodium Hyaluronate

Superscreen Daily Moisturizer Broad Spectrum SPF 40

Inactive ingredients Water, Cartamus Tinctorius (safflower) Olesomes, Glycerin, C12-15 Alkyl Benzoate, Polyester-7, Ammonium Acryloyldimethyldimethyltaurate/VP Copolymer, Neopentyl Glycol Diheptanoate, Carthamus Tinctorius (Safflower) Seedcake extract, Aphanizomenon Flos-Aquae Extract, Inulin Lauryl Carbamate, Xanthan Gum, Biosaccharide Gum-4, Cerium Oxide, Platinum Powder, 1,2-hexanediol, Ehtylhexylglycerin, Phenethyl Alcohol, Chlorphenesin

Zinc screen Broad Spectrum Sunscreen SPF 40

Inactive Ingredients

Water, Tetradecane, Cetearyl Nonanoate, Ethylhexyl Palmitate, Caprylic/Capric Triglyceride, Isopropyl Myristate, Glycerin, Polyglyceryl-3 Diisostearate, Mica, Propanediol, Disteardimonium Hectorite, Gluconolactone, Polyglyceryl-6 Polyricinoleate, Brassica Campestris/Aleurites Fordi Oil Copolymer, Polyhydrostearic Acid, Sodium Chloride, Magnesium Sulfate, Fructose, Octyldodecyl Oleate, Tocopherol, Cocos Nucifera (Coconut) Fruit Extract, Sodium Benzoate, Iron oxides (CI 77492), Dodecane, Hexadecane, Titanium Dioxide (CI 77891), Withania Somnifera Flower Extract, Iron Oxides (CI 77491), Vaccinium Angustifolia (Blueberry) Fruit Extract, Silica, Calcium Gluconate

PACKAGE LABEL

Prep & Prime

SPF Mini Set

Give your skin daily hydration with this sample set of moisturizing SPFs and multitasking primers

Mineral Sheerscreen SPF 30 (10 ml)

Superscreen Daily Moisturizer SPF 40 (10 ml)

Glowscreen SPF 40 (10 ml)

Zincscreen 100% Mineral Lotion SPF 40 (10 ml)

Glow screen SPF 40

Inactive Ingredients
Water, Propanediol, Butyloctyl Salicylate, Glycerin, C12-15 Alkyl Benzoate, Polymethylsilsesquioxane, Niacinamide, Glyceryl Stearate Citrate, Bismuth Oxychloride, Mica, Titanium Dioxide, Lauryl Lactate, Isododecane, Isodecyl Neopentanoate, Glyceryl Stearate, Diisopropyl Sebacate, Cetyl Phosphate, Caprylic/Capric Triglyceride, Coco-Caprylate, Ethylhexyl Hydroxystearate, Butylene Glycol, Arginine, Hydroxyacetophenone, Caprylyl Glycol, 1,2-Hexanediol, Iron Oxides, Sodium Hyaluronate, Chlorphenesin, Acrylates/C10-30 Alkyl Acrylate Crosspolymer, Trisodium Ethylenediamine Disuccinate, Phospholipids, Limonium Gerberi Extract, Leuconostoc/Radish Root Ferment Filtrate, Theobroma Cacao (Cocoa) Seed Extract, Pantothenic Acid, Tocopherol, Helianthus Annuus (sunflower) Seed Oil, Ferulic Acid

Prep & Prime SPF Mini Set

Prep & Prime

SPF Mini Set

Give your skin daily hydration with this sample set of moisturizing SPFs and multitasking primers

Mineral sheerscreen SPF 30 (10 ml)

Superscreen Daily Moisturizer SPF 40 (10 ml)

Glowscreen SPF 40 (10 ml)

Zincscreen 100% Mineral Lotion SPF 40 (10 ml)

Mineral Sheerscreen Broad Spectrum Sunscreen SPF 30

Mineral Sheerscreen SPF 30

SPF 30

100% Mineral

Broad Spectrum Sunscreen

SPF 30 PA+++

0.34 fl. oz. / 10 ml.

Superscreen Daily Moisturizer SPF 40

SPF 40

Broad Spectrum Sunscreen SPF 40 PA+++

0.34 fl. oz. / 10 ml

Glowscreen SPF 40

Broad Spectrum Sunscreen

SPF 40 PA+++

0.34 fl. oz. / 10 ml

Zincscreen 100% Mineral Lotion SPF 40

Zincscreen 100% Mineral Lotion

SPF 40

Broad Spectrum Sunscreen SPF 40 PA+++

0.34 fl.oz. / 10ml